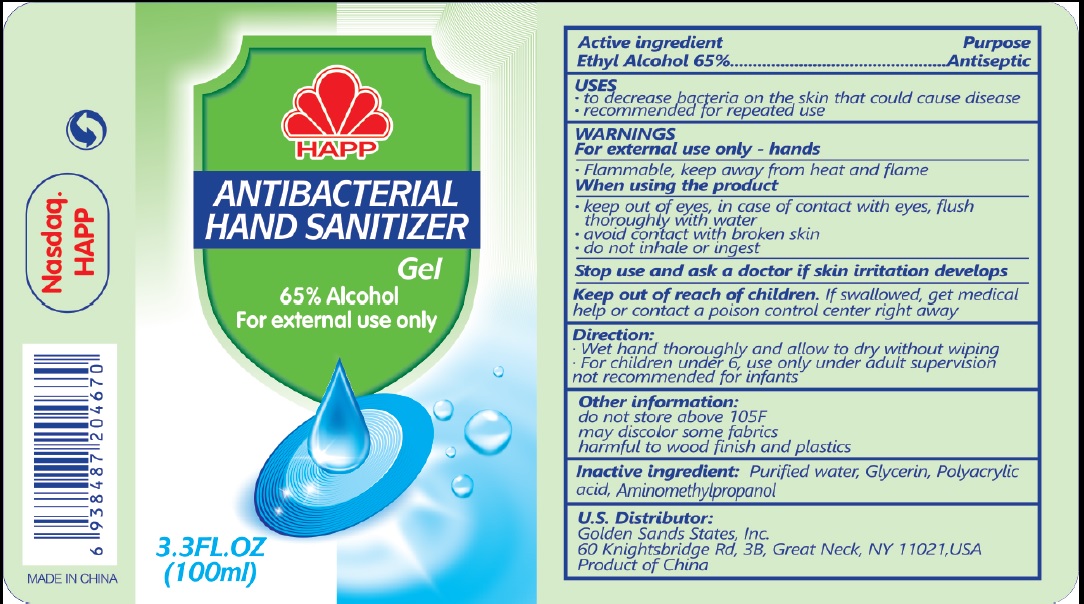 DRUG LABEL: Happ Hand Sanitizer
NDC: 76735-001 | Form: GEL
Manufacturer: Fujian Happiness Biotech Technology Co., Ltd.
Category: otc | Type: HUMAN OTC DRUG LABEL
Date: 20200702

ACTIVE INGREDIENTS: ALCOHOL 65 mL/100 mL
INACTIVE INGREDIENTS: GLYCERIN; POLYACRYLIC ACID (250000 MW); WATER; AMINOMETHYLPROPANOL

Active Ingredient

Ethyl Alcohol 65% v/v.

Purpose

Antiseptic

Uses

- to decrease bacteria on the skin that could cause disease
- recommended for repeated use

Warnings

For external use only - hands

- Flammable, keep away from heat and flame

When using the product

- keep out of eyes, in case of contact with eyes, flush thoroughly with water
- avoid contact with broken skin
- do not inhale or ingest

Stop use and ask a doctor if skin irritation develops.

Keep out of reach of children. If swallowed, get medical help or contact a Poison Control Center right away.

Directions

- Wet hand thoroughly and allow to dry without wiping
- For children under 6, use only under adult supervision
- not recommended for infants

Inactive ingredients

Purified water, Glycerin, Polyacrylic acid, Aminomethylpropanol